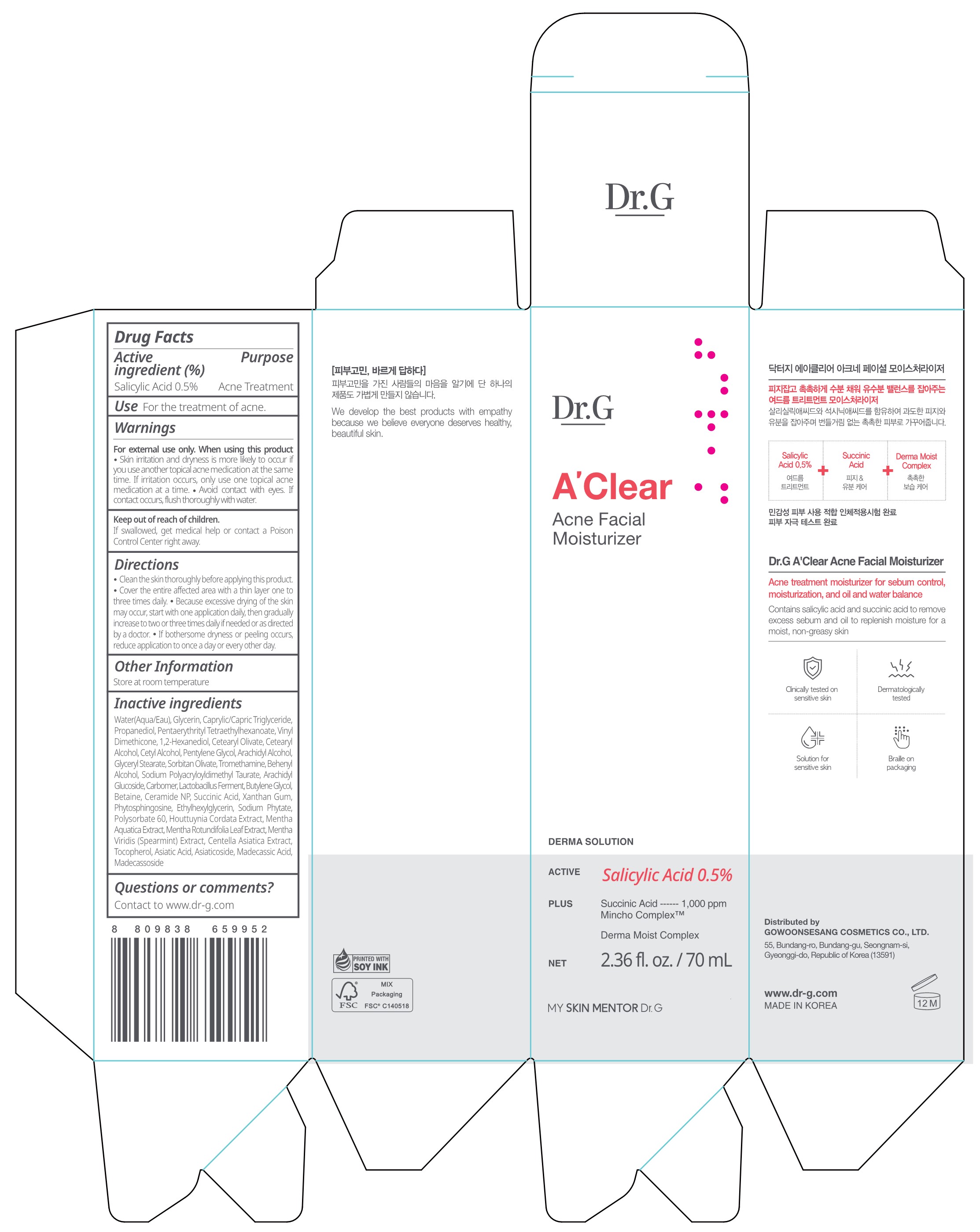 DRUG LABEL: Dr.G A CLEAR ACNE FACIAL MOISTURIZER
NDC: 51621-413 | Form: CREAM
Manufacturer: GOWOONSESANG COSMETICS CO., LTD.
Category: otc | Type: HUMAN OTC DRUG LABEL
Date: 20250320

ACTIVE INGREDIENTS: SALICYLIC ACID 0.5 g/100 mL
INACTIVE INGREDIENTS: CETEARYL ALCOHOL; SODIUM PHYTATE; MENTHA SPICATA; ASIATICOSIDE; PENTAERYTHRITYL TETRAETHYLHEXANOATE; ARACHIDYL ALCOHOL; SODIUM POLYACRYLOYLDIMETHYL TAURATE; XANTHAN GUM; CENTELLA ASIATICA TRITERPENOIDS; POLYSORBATE 60; ASIATIC ACID; PROPANEDIOL; MADECASSIC ACID; CETEARYL OLIVATE; TROMETHAMINE; GLYCERYL STEARATE; MENTHA X ROTUNDIFOLIA LEAF; CETYL ALCOHOL; BUTYLENE GLYCOL; 1,2-HEXANEDIOL; HOUTTUYNIA CORDATA FLOWERING TOP; TOCOPHEROL; CAPRYLIC/CAPRIC TRIGLYCERIDE; BEHENYL ALCOHOL; ARACHIDYL GLUCOSIDE; CARBOMER; BETAINE; ETHYLHEXYLGLYCERIN; MADECASSOSIDE; GLYCERIN; WATER; CERAMIDE NP; SUCCINIC ACID; PHYTOSPHINGOSINE; PENTYLENE GLYCOL; SORBITAN OLIVATE

Active ingredient

Salicylic Acid 0.5%

Purpose

Acne Treatment

Use

For the treatment of acne.

Warnings

For external use only. When using this product

- Skin irritation and dryness is more likely to occur if you use another topical acne medication at the same time. If irritation occurs, only use one topical acne medication at a time.
- Avoid contact with eyes. If contact occurs, flush thoroughly with water.

Keep out of reach of children.

If swallowed, get medical help or contact a Poison Control Center right away.

Directions

- Clean the skin thoroughly before applying this product.
- Cover the entire affected area with a thin layer one to three times daily.
- Because excessive drying of the skin may occur, start with one application daily, then gradually increase to two or three times daily if needed or as directed by a doctor.
- If bothersome dryness or peeling occurs, reduce application to once a day or every other day.

Other Information

Store at room temperature

Inactive ingredients

Water(Aqua/Eau), Glycerin, Caprylic/Capric Triglyceride, Propanediol, Pentaerythrityl Tetraethylhexanoate, Vinyl Dimethicone, 1,2-Hexanediol, Cetearyl Olivate, Cetearyl Alcohol, Cetyl Alcohol, Pentylene Glycol, Arachidyl Alcohol, Glyceryl Stearate, Sorbitan Olivate, Tromethamine, Behenyl Alcohol, Sodium Polyacryloyldimethyl Taurate, Arachidyl Glucoside, Carbomer, Lactobacillus Ferment, Butylene Glycol, Betaine, Ceramide NP, Succinic Acid, Xanthan Gum, Phytosphingosine, Ethylhexylglycerin, Sodium Phytate, Polysorbate 60, Houttuynia Cordata Extract, Mentha Aquatica Extract, Mentha Rotundifolia Leaf Extract, Mentha Viridis (Spearmint) Extract, Centella Asiatica Extract, Tocopherol, Asiatic Acid, Asiaticoside, Madecassic Acid, Madecassoside

Questions or comments?

Contact to www.dr-g.com